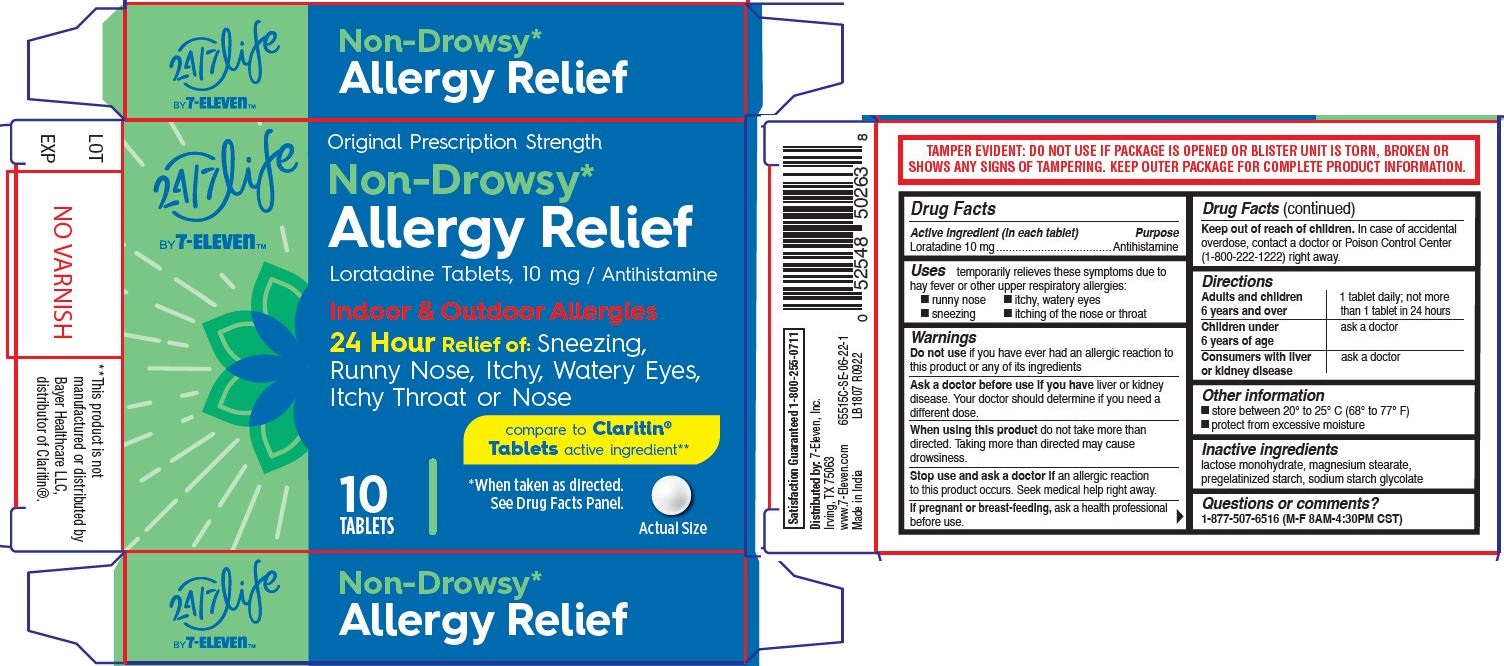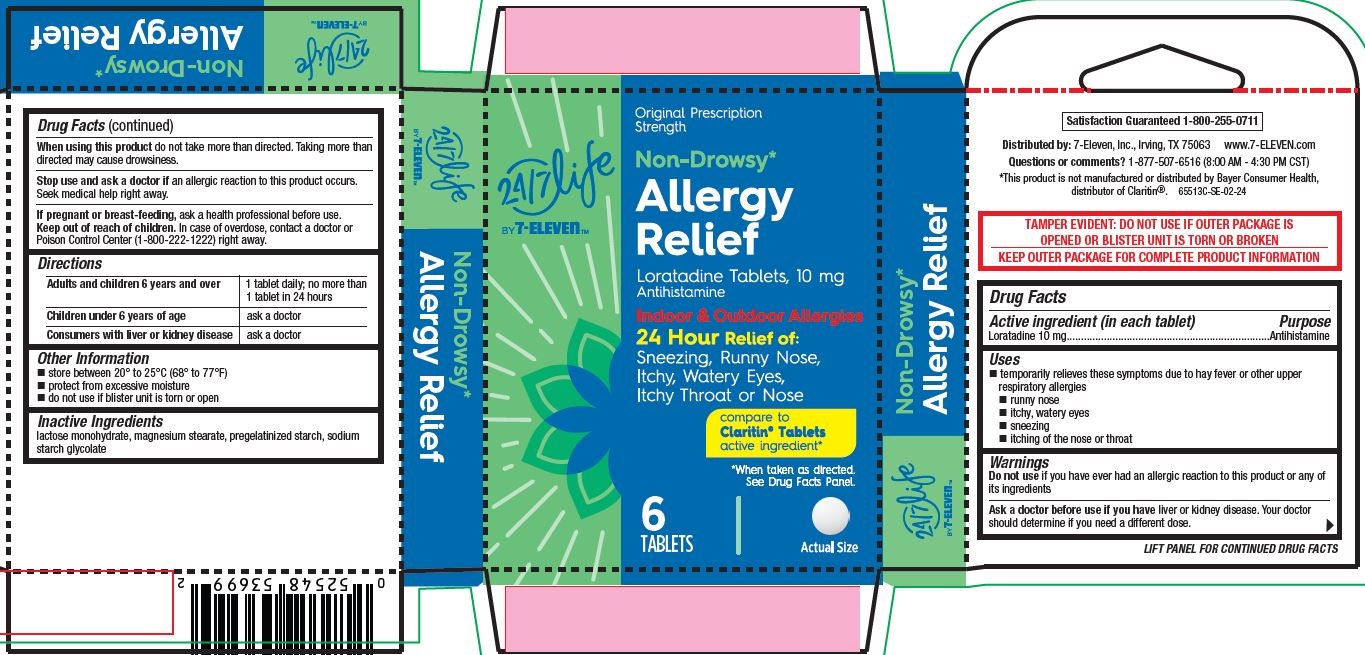 DRUG LABEL: Non-Drowsy Allergy Relief, 24-7 Life
NDC: 66715-6551 | Form: TABLET
Manufacturer: Lil' Drug Store Products, Inc.
Category: otc | Type: HUMAN OTC DRUG LABEL
Date: 20240410

ACTIVE INGREDIENTS: LORATADINE 10 mg/1 1
INACTIVE INGREDIENTS: LACTOSE MONOHYDRATE; SODIUM STARCH GLYCOLATE TYPE A POTATO; MAGNESIUM STEARATE; STARCH, CORN

Non-Drowsy Allergy Relief, 24-7 Life by 7-ElevenTM

Drug Facts

Active ingredient

Active ingredient (in each tablet)

Loratadine 10 mg

Purpose

Antihistamine

Uses

Uses temporarily relieves these symptoms due to hay fever or other upper respiratory allergies:

- runny nose
- itchy, watery eyes
- sneezing
- itching of the nose or throat

Warnings

Do not use if you have ever had an allergic reaction to this product or any of its ingredients

Ask a doctor before use if you have liver or kidney disease. Your doctor should determine if you need a different dose.

When using this product do not take more than directed. Taking more than directed may cause drowsiness.

Stop use and ask a doctor if an allergic reaction to this product occurs. Seek medical help right away.

If pregnant or breast-feeding, ask a health professional before use.

Keep out of reach of children. In case of accidental overdose, contact a doctor or Poison Control Center (1-800-222-1222) right away.

Directions

Adults and children 6 years and over | 1 tablet daily; not more than 1 tablet in 24 hours
Children under 6 years of age | ask a doctor
Consumers with liver or kidney disease | ask a doctor

Other information

- store between 20° to 25° C (68° to 77° F)
- protect from excessive moisture

Inactive ingredients

lactose monohydrate, magnesium stearate, pregelatinized starch, sodium starch glycolate

Questions or comments? 1-877-507-6516 (M-F 8AM-4:30PM CST)

Non-Drowsy Allergy Relief, 10ct, 24/7 Life BY 7-ELEVEN - PDP/Package

24/7 Life BY 7-ELEVEN

Original Prescription Strength

Non-Drowsy*
Allergy Relief

Loratadine Tablets, 10 mg / Antihistamine

Indoor & Outdoor Allergies
24 Hour Relief of: Sneezing,
Runny Nose, Itchy, Watery Eyes,
Itchy Throat or Nose

compare to Claritin®
Tablets active ingredient**

10

TABLETS

*When taken as directed.

See Drug Facts Panel.

[tablet image]

Actual Size

Non-Drowsy Allergy Relief 6ct, 24/7 Life BY 7-ELEVENTM - PDP/Package

24/7 Life BY 7-ELEVEN

Original Prescription

Strength

Non-Drowsy*
Allergy

Relief

Loratadine Tablets, 10 mg

Antihistamine

Indoor & Outdoor Allergies
24 Hour Relief of:

Sneezing, Runny Nose,

Itchy, Watery Eyes,
Itchy Throat or Nose

compare to Claritin® Tablets

active ingredient*

6

TABLETS

*When taken as directed.

See Drug Facts Panel.

[tablet image]

Actual Size